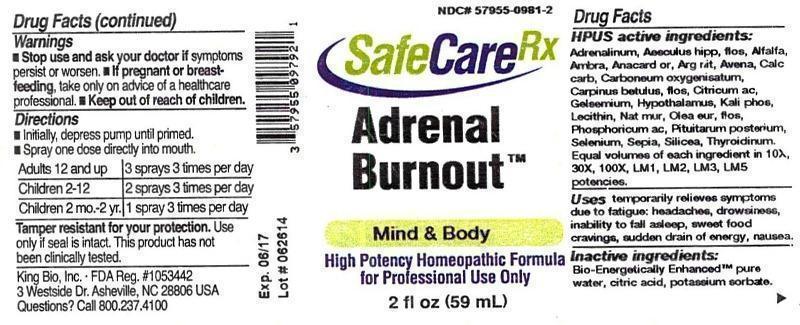 DRUG LABEL: Adrenal Burnout
NDC: 57955-0981 | Form: LIQUID
Manufacturer: King Bio Inc.
Category: homeopathic | Type: HUMAN OTC DRUG LABEL
Date: 20141210

ACTIVE INGREDIENTS: EPINEPHRINE 10 [hp_X]/59 mL; AESCULUS HIPPOCASTANUM FLOWER 10 [hp_X]/59 mL; ALFALFA 10 [hp_X]/59 mL; AMBERGRIS 10 [hp_X]/59 mL; SEMECARPUS ANACARDIUM JUICE 10 [hp_X]/59 mL; SILVER NITRATE 10 [hp_X]/59 mL; AVENA SATIVA FLOWERING TOP 10 [hp_X]/59 mL; OYSTER SHELL CALCIUM CARBONATE, CRUDE 10 [hp_X]/59 mL; CARBON MONOXIDE 10 [hp_X]/59 mL; CARPINUS BETULUS FLOWERING TOP 10 [hp_X]/59 mL; ANHYDROUS CITRIC ACID 10 [hp_X]/59 mL; GELSEMIUM SEMPERVIRENS ROOT 10 [hp_X]/59 mL; BOS TAURUS HYPOTHALAMUS 10 [hp_X]/59 mL; POTASSIUM PHOSPHATE, DIBASIC 10 [hp_X]/59 mL; EGG PHOSPHOLIPIDS 10 [hp_X]/59 mL; SODIUM CHLORIDE 10 [hp_X]/59 mL; OLEA EUROPAEA FLOWER 10 [hp_X]/59 mL; PHOSPHORIC ACID 10 [hp_X]/59 mL; SUS SCROFA PITUITARY GLAND 10 [hp_X]/59 mL; SELENIUM 10 [hp_X]/59 mL; SEPIA OFFICINALIS JUICE 10 [hp_X]/59 mL; SILICON DIOXIDE 10 [hp_X]/59 mL; THYROID, UNSPECIFIED 10 [hp_X]/59 mL
INACTIVE INGREDIENTS: WATER; CITRIC ACID MONOHYDRATE; POTASSIUM SORBATE

Adrenal Burnout™

Warnings

- Stop use and ask your doctor if symptoms persist or worsen.
- If pregnant or breast-feeding, take only on advice of a healthcare professional.

- Keep out of reach of children

DOSAGE AND ADMINISTRATION

- Initially, depress pump until primed.
- Spray one dose directly into mouth.
- Adults 12 and up: 3 sprays 3 times per day.
- Children (2-12 years): 2 sprays 3 times per day.
- Children (2 mo.-2 years): 1 spray 3 times per day.

OTHER SAFETY INFORMATION

Tamper resistant for your protection. Use only if safety seal is intact. This product has not been clinically tested.

ACTIVE INGREDIENT

HPUS active ingredients: Adrenalinum, Aesculus hippocastanum, flos, Alfalfa, Ambra grisea, Anacardium orientale, Argentum nitricum, Avena sativa, Calcarea carbonica, Carboneum oxygenisatum, Carpinus betulus, flos, Citricum acidum, Gelsemium sempervirens, Hypothalamus, Kali phosphoricum, Lecithin, Natrum muriaticum, Olea europaea, flos, Phosphoricum acidum, Pituitarum posterium, Selenium metallicum, Sepia, Silicea, Thyroidinum. Equal volumes of each ingredient in 10X, 30X, 100X, LM1, LM2, LM3, LM5 potencies.

PURPOSE

Uses temporarily relieves symptoms due to fatigue: headaches, drowsiness, inability to fall asleep, sweet food cravings, sudden drain of energy, nausea.

Inactive Ingredients:

Bio-Energetically Enhanced™ pure water, citric acid and potassium sorbate.

INDICATIONS AND USAGE

Uses temporarily relieves symptoms due to fatigue:

- headaches
- drowsiness
- inability to fall asleep
- sweet food cravings
- sudden drain of energy
- nausea